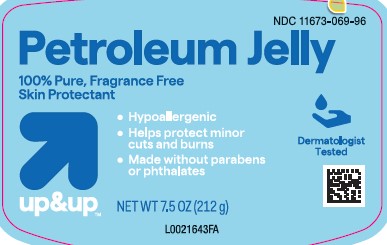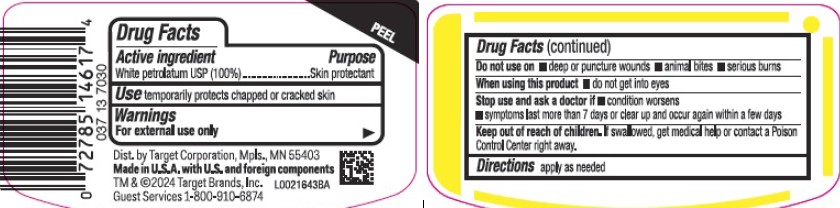 DRUG LABEL: Pure petroleum
NDC: 11673-069 | Form: JELLY
Manufacturer: Target Corporation
Category: otc | Type: HUMAN OTC DRUG LABEL
Date: 20260218

ACTIVE INGREDIENTS: PETROLATUM 1 g/1 g

Up & Up 069.001/069AA
Petroleum Jelly

Active ingredient

White petrolatum USP (100%)

Purpose

Skin protectant

Use

- temporarily protects chapped or cracked skin

Warnings

For external use only

Do not use on

- deep or puncture wounds
- animal bites
- serious burns

When using this product

- do not get into eyes

Stop use and ask a doctor if

- condition worsens
- symptoms last more than 7 days or clear up and occur again within a few days

Keep out of reach of children.

If swallowed, get medical help or contact a Poison Control Center right away.

Directions

apply as needed

Inactive Ingredients

None

Adverse Reactions

Dist. by Target Corporation, Mpls., MN 55403

Made in U.S.A with U.S. and foreign components

TM & ©2024 Target Brands, Inc.

Guest Services 1-800-910-6874

Principal display panel

NDC 11673-069-96

Petroleum Jelly

100% Pure, Fragrance Free

Skin Protectant

- Hypoallergenic
- Helps protect minor cuts and burns
- Made without parabens or phthalates

Dermatologist Tested

up & up™

NET WT 7.5 OZ (212 g)